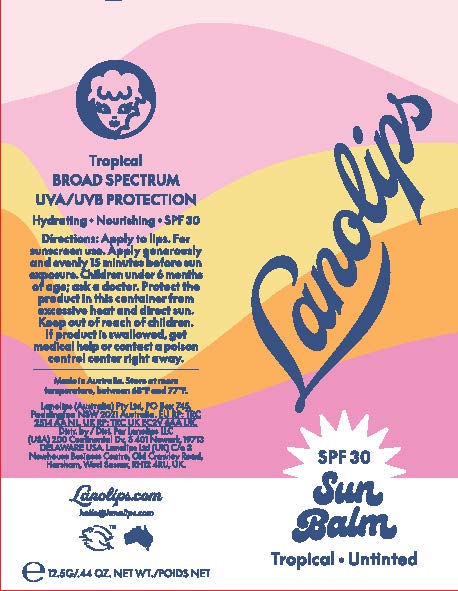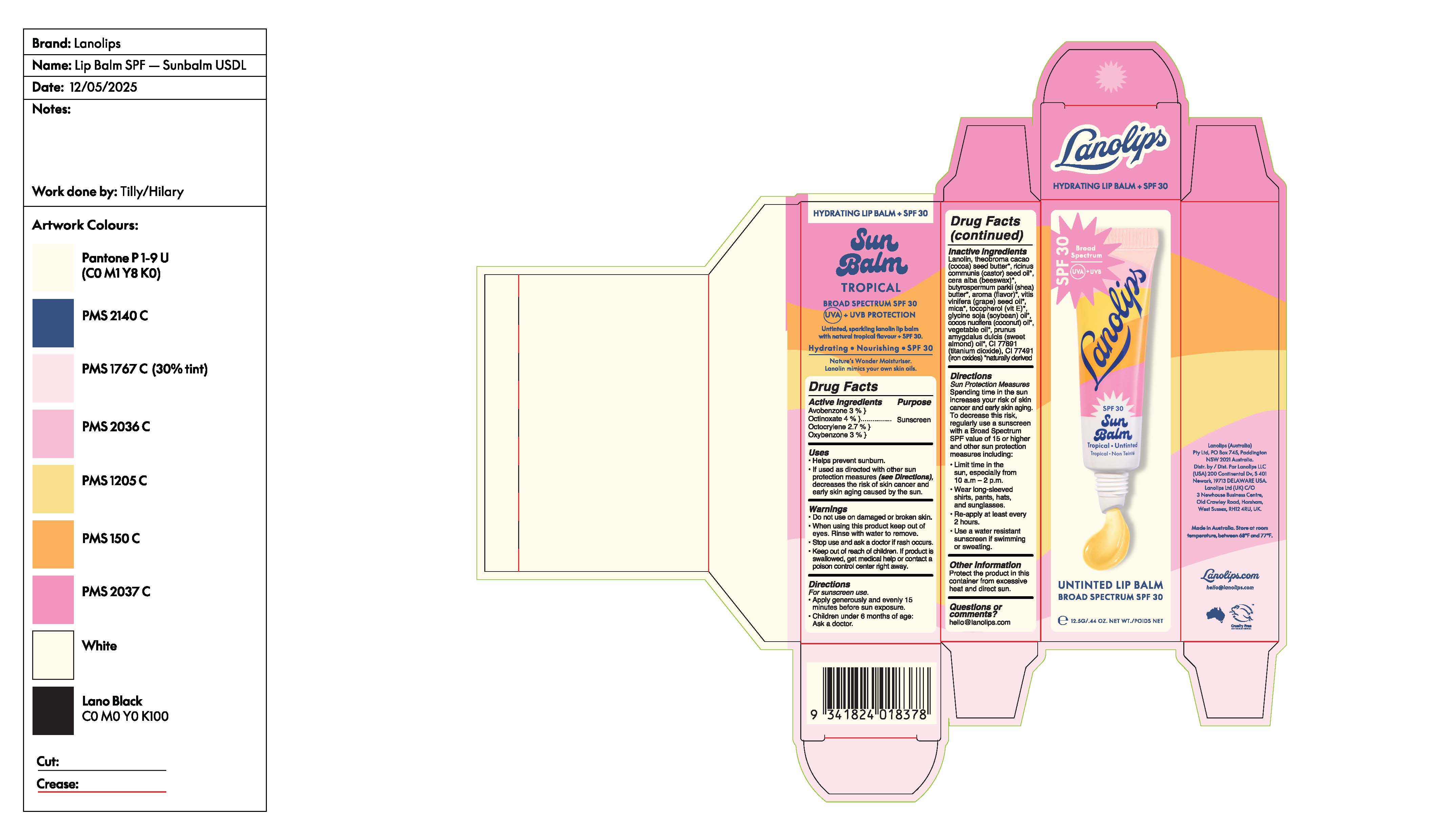 DRUG LABEL: Lanolips Sun Balm Tropical Untinted Lip Balm Broad Spectrum SPF30
NDC: 70157-035 | Form: CREAM
Manufacturer: Baxter Laboratories Pty. Ltd.
Category: otc | Type: HUMAN OTC DRUG LABEL
Date: 20251118

ACTIVE INGREDIENTS: OCTINOXATE 4 g/100 g; AVOBENZONE 3 g/100 g; OXYBENZONE 3 g/100 g; OCTOCRYLENE 2.7 g/100 g
INACTIVE INGREDIENTS: GLYCINE MAX (SOYBEAN) OIL; SHEA BUTTER; VITIS VINIFERA (GRAPE) SEED OIL; TOCOPHEROL; WHITE WAX; CORN OIL; TITANIUM DIOXIDE; PRUNUS AMYGDALUS DULCIS (SWEET ALMOND) OIL; FERRIC OXIDE RED; COCOS NUCIFERA (COCONUT) OIL; LANOLIN; COCOA BUTTER; RICINUS COMMUNIS (CASTOR) SEED OIL

Lanolips Sun Balm Tropical Untinted Lip Balm Broad Spectrum SPF30

Active Ingredients Purpose

Avobenzone 3%.....Sunscreen

Octinoxate 4%

Octocrylene 2.7%

Oxybenzone 3%

Uses

- Helps prevent sunburn
- If used as directed with other sun protection measures (see Directions), decreases the risk of skin cancer and early skin aging caused by the sun.

KEEP OUT OF REACH OF CHILDREN

If swallowed, get medical help or contact a Poison Control Center right away.

Stop use and ask a doctor if rash occurs.

WARNINGS

For external use only

Do not use on damaged or broken skin.

DOSAGE AND ADMINISTRATION

Apply liberally 15 minutes before sun exposure. Use a water resistant sunscreen if swimming or sweating.
Sun Protection Measures. Spending time in the sun increases your risk of skin cancer and early skin aging. To decrease this risk, regularly use a sunscreen with a Broad Spectrum SPF value of 15 or higher and other sun protection measures including:

- Limit time in the sun, especially from 10 a.m.- 2 p.m.
- Wear long-sleeved shirts, pants, hats, and sunglasses.
- Children under 6 months: Ask a doctor.
- Use a water resistant sunscreen if swimming or sweating

Inactive Ingredients

Lanolin, Theobroma cacao (cocoa) seed butter, ricinus communis (castor) seed oil, cera alba (beeswax), butyrospermum parkii (shea) butter, aroma (flavor), vitis vinifera (grape) seed oil, mica, tocopherol (vit E), glycine soja (soybean) oil, cocos nucifera (coconut) oil, vegetable oil, prunus amygdalus dulcis (sweet almond) oil, CI 77891 (titanium dioxide), CI 77491 (iron oxides)

PACKAGE LABEL

Lanolips

SPF 30

Sun Balm Tropical

untinted Lip Balm

12.5G/ .44 OZ Net Wt. Poids Net